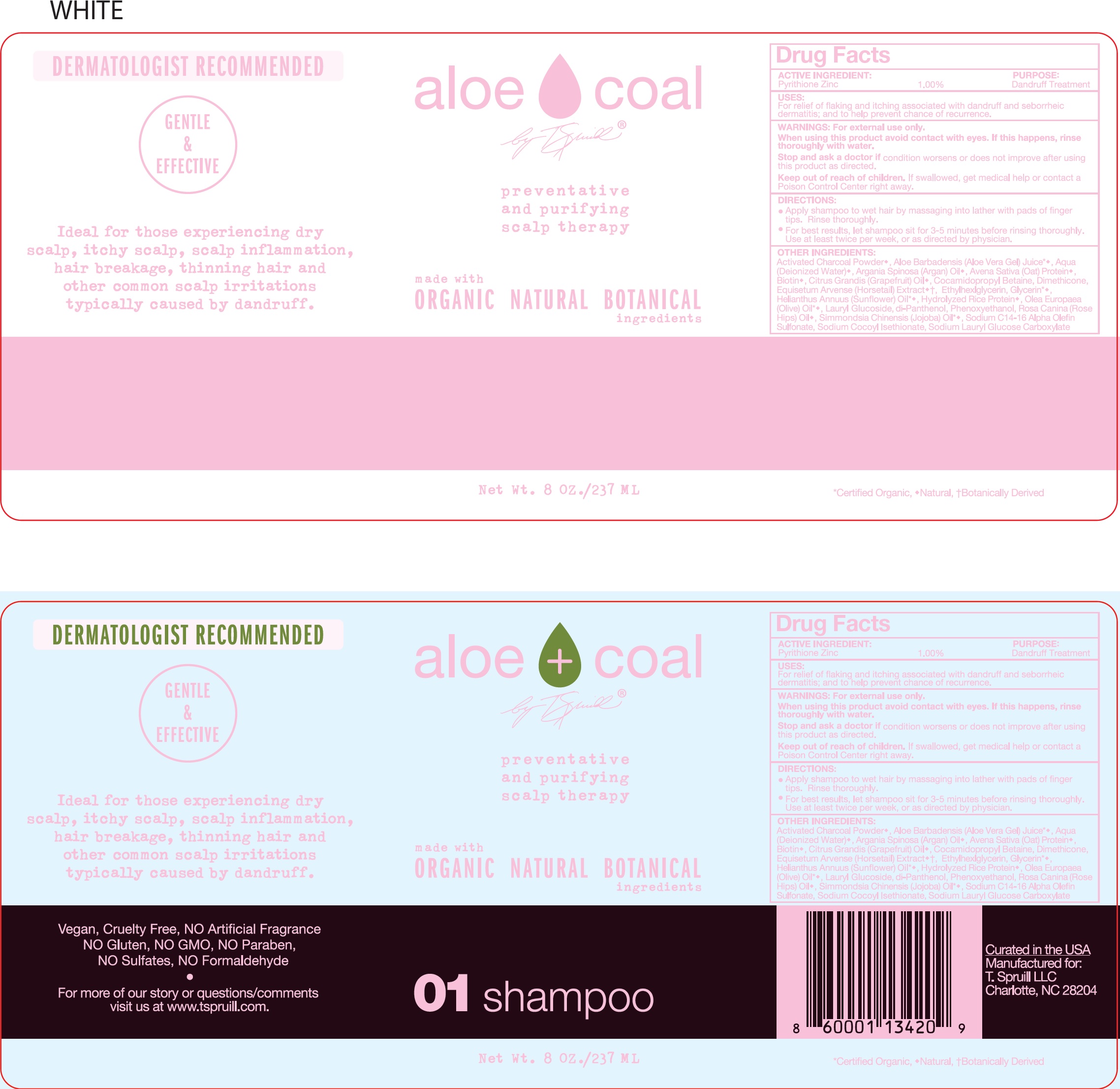 DRUG LABEL: Aloe Coal 01
NDC: 73324-091 | Form: LIQUID
Manufacturer: T. SPRUILL, LLC
Category: otc | Type: HUMAN OTC DRUG LABEL
Date: 20231111

ACTIVE INGREDIENTS: PYRITHIONE ZINC 10 mg/1 mL
INACTIVE INGREDIENTS: ALOE VERA LEAF; WATER; ARGAN OIL; OAT; BIOTIN; GRAPEFRUIT; COCAMIDOPROPYL BETAINE; DIMETHICONE; EQUISETUM ARVENSE BRANCH; ETHYLHEXYLGLYCERIN; GLYCERIN; HELIANTHUS ANNUUS FLOWERING TOP; OLEA EUROPAEA (OLIVE) OIL UNSAPONIFIABLES; LAURYL GLUCOSIDE; PHENOXYETHANOL; ROSA CANINA FRUIT; JOJOBA OIL; SODIUM COCOYL ISETHIONATE

Aloe + Coal 01 Shampoo

ACTIVE INGREDIENT:

Pyrithione Zinc 1.00%

PURPOSE

Dandruff Treatment

USES:

For relief of flaking and itching associated with dandruff and seborrheic dermatitis and to help prevent chance of recurrence.

WARNINGS

For external use only.

When using this product

avoid contact with eyes. If this happens, rinse thoroughly with water.

Stop and ask a doctor

if condition worsens or does not improve after using this product as directed.

Keep out of reach of children.

If swallowed, get medical help or contact a Poison Control Center right away.

DIRECTIONS:

- Apply shampoo to wet hair by massaging into lather with pads of finger tips. Rinse thoroughly.
- For best results, let shampoo sit for 3-5 minutes before rinsing thoroughly. Use a least twice per week, or as directed by physician.

OTHER INGREDIENTS:

Activated Charcoal Powder, Aloe Barbadensis (Aloe Vera Gel) Juice, Aqua (Deionized Water), Argania Spinosa (Argan) Oil, Avena Sativa (Oat) Protein, Biotin, Citrus Grandis (Grapefruit) Oil, Cocamidopropyl Betaine, Dimethicone, Equisetum Arvense (Horsetail) Extract, Ethylhexylglycerin, Glycerin, Helianthus Annuus (Sunflower) Oil, Hydrolyzed Rice Protein, Olea Europaea (Olive) Oil, Lauryl Glucoside, di-Panthenol, Phenoxyethanol, Rosa Canina (Rose Hips) Oil, Simmondsia Chinensis (Jojoba) Oil, Sodium C14-16 Alpha Olefin Sulfonate, Sodium Cocoyl Isethionate, Sodium Lauryl Glucose Carboxylate